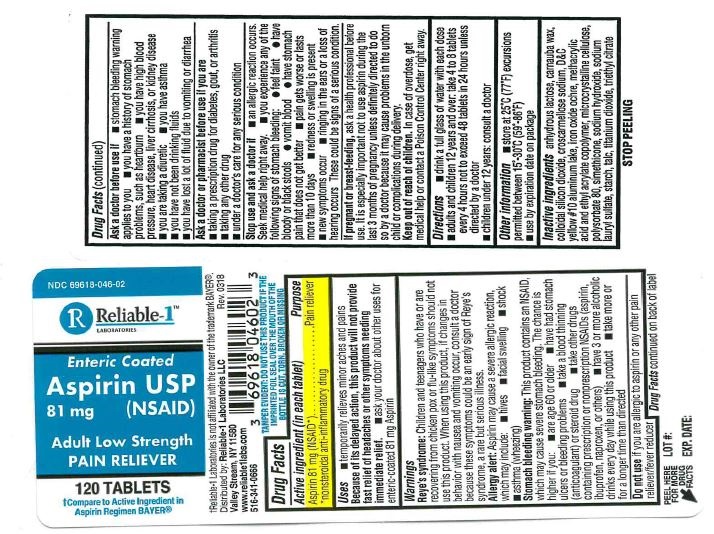 DRUG LABEL: Aspirin 81 mg Enteric Coated
NDC: 69618-046 | Form: TABLET
Manufacturer: Reliable 1 Laboratories LLC
Category: otc | Type: HUMAN OTC DRUG LABEL
Date: 20230329

ACTIVE INGREDIENTS: ASPIRIN 81 mg/1 1
INACTIVE INGREDIENTS: D&C YELLOW NO. 10; DIMETHICONE; TALC; IRON; METHACRYLIC ACID - ETHYL ACRYLATE COPOLYMER (1:1) TYPE A; MICROCRYSTALLINE CELLULOSE; POLYSORBATE 80; CROSCARMELLOSE SODIUM; CARNAUBA WAX; SILICON DIOXIDE; SODIUM HYDROXIDE; SODIUM LAURYL SULFATE; STARCH, CORN; TITANIUM DIOXIDE; TRIETHYL CITRATE

Aspirin USP 81mg Enteric Coated Tablet

Active ingredients (in each tablet)

Aspirin 81 mg (NSAID*)

*nonsteroidal anti-inflammatory drug

Purpose

Pain reliever

Uses

- temporarily relieves minor aches and pains

Because of its delayed action, this product will not provide fast relief of headaches or other symptoms needing immediate relief.

- ask your doctor about other uses for enteric-coated 81 mg Aspirin

Warnings

Reye's syndrome: Children and teenagers who have or are recovering from chicken pox or flu-like symptoms should not use this product. When using this product, if changes in behavior with nausea and vomiting occur, consult a doctor because these symptons could be an early sign of Reye's syndrome, a rare but serious illness.

Allergy alert: Aspirin may cause a severe allergic reaction, which any include:

- hives
- facial swelling
- shock
- asthma (wheezing)

Stomach bleeding warning: This product contains NSAID, which may cause severe stomach bleeding. The chance is higher if you:

are age 60 or older
have had stomach ulcers or bleeding problems
take a blood thinning (anticoagulant) or steroid drug
take other drugs containing prescription or nonprescription NSAIDs (aspirin, ibuprofen, naproxen, or others)
have 3 or more alcoholic drinks every day while using this product
take more or for a longer time than directed

Do not use if you are allergic to aspirin or any other pain reliever/fever reducer

Ask a doctor before use if

- stomach bleeding warning applies to you
- you have a history of stomach problems, such as heartburn
- you have high blood pressure, heart disease, liver cirrhosis, or kidney disease
- you are taking a diuretic
- you have asthma
- you have not been dirinking fluids
- you have lost a lot of fluid due to vomiting or diarrhea

Ask a doctor or pharmacist before use if you are

- taking a prescription drug for diabetes, gout, or arthritis
- taking any other drug
- under a doctor's care for any serious condition

Stop use and ask a doctor if

- an allergic reaction occurs. Seek medical help right away.
- you experience any of the following signs of stomach bleeding:

feel faint

have bloody or black stools

vomit blood

have stomach pain that does not get better

- pain gets worse or lasts more than 10 days
- redness or swelling is present
- new symptoms occur
- ringing in the ears or a loss of hearing occurs

These could be sings of a serious condition.

PREGNANCY OR BREAST FEEDING

If pregnant or brest-feeding, ask a health professional before use. It is especially important not to use aspirin during the last 3 months of pregnancy unless definitely directed to do so by a doctor because it may cause problems in the unborn child or conplications during delivery.

Keep out of reach of children. In case of overdose, get medical help or contact a Poison Control Center right away.

Directions

- drink a full glass of water with each dose
- adults and children 12 years and over: take 4 to 8 tablets every 4 hours not to exceed 48 tablets in 24 hours unless directed by a doctor
- children under 12 years: consult a doctor

Other information

- store at 25ºC (77ºF) excursions permitted between 15º-30ºC (59º-86ºF)
- use by expiration date on package

Inactive ingredients

anhydrous lactose, carnauba wax, colloidal silicon dioxide, croscarmellose sodium, D&C yellow #10 aluminum lake, iron oxide ochre, methacrylic acid and ethyl acrylate copolymer, microcrystalline cellulose, polysorbate 80, simethicone, sodium hydroxide, sodium lauryl sulfate, starch, talc, titanium dioxide, triethyl citrate

Questions or comments?

call 516-341-0666, 8:30 am - 4:30 pm ET, Monday - Friday

PACKAGE LABEL

NDC 69618-046-10

Enteric Coated

Aspirin USP 81mg (NSAID

Adult Low Strength

PAIN RELIEVER

THIS PACKAGE FOR HOUSEHOLDS WITHOUT YOUNG CHILDREN

1000 TABLETS